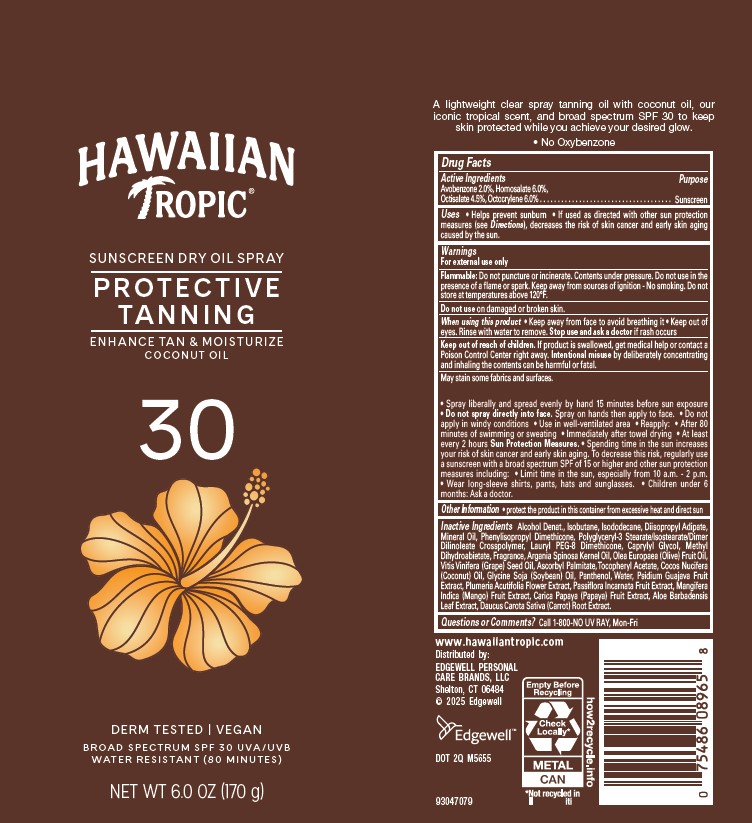 DRUG LABEL: HAWAIIAN TROPIC
NDC: 63354-613 | Form: AEROSOL, SPRAY
Manufacturer: Edgewell Personal Care Brands LLC
Category: otc | Type: HUMAN OTC DRUG LABEL
Date: 20250928

ACTIVE INGREDIENTS: AVOBENZONE 2 g/100 g; HOMOSALATE 6 g/100 g; OCTOCRYLENE 6 g/100 g; OCTISALATE 4.5 g/100 g
INACTIVE INGREDIENTS: ALPHA-TOCOPHEROL ACETATE; ASCORBYL PALMITATE; ALOE VERA LEAF; PASSIFLORA INCARNATA FRUIT; PAPAYA; CARROT; MANGO; ISODODECANE; CAPRYLYL GLYCOL; PANTHENOL; PLUMERIA RUBRA FLOWER; LAURYL PEG-8 DIMETHICONE (300 CPS); SOYBEAN OIL; METHYL DIHYDROABIETATE; GRAPE SEED OIL; OLIVE OIL; GUAVA; WATER; ARGAN OIL; ISOBUTANE; DIISOPROPYL ADIPATE; MINERAL OIL; COCONUT OIL; GLYCERYL OLEATE; ALCOHOL

Active Ingredients

Avobenzone 2.0%, Homosalate 6.0%, Octisalate 4.5%, Octocrylene 6.0%

Purpose

Sunscreen

Uses

• Helps prevent sunburn • If used as directed with other sun protection measures (see Directions), decreases the risk of skin cancer and early skin aging caused by the sun.

Warnings

For external use only

Flammable: Do not puncture or incinerate. Contents under pressure. Do not use in the presence of a flame or spark. Keep away from sources of ignition - No smoking. Do not store at temperatures above 120°F.

May stain some fabrics and surfaces.

Do not use

on damaged or broken skin.

When using this product

• Keep away from face to avoid breathing it • Keep out of eyes. Rinse with water to remove.

Stop use and ask a doctor

if rash occurs

Keep out of reach of children.

If product is swallowed, get medical help or contact a Poison Control Center right away. Intentional misuse by deliberately concentrating and inhaling the contents can be harmful or fatal.

Directions

• Shake well • Hold container 4 to 6 inches from the skin to apply • Spray liberally and spread evenly by hand 15 minutes before sun exposure • Do not spray directly into face. Spray on hands then apply to face. • Do not apply in windy conditions • Use in well-ventilated area • Reapply: • After 80 minutes of swimming or sweating • Immediately after towel drying • At least every 2 hours Sun Protection Measures. • Spending time in the sun increases your risk of skin cancer and early skin aging. To decrease this risk, regularly use a sunscreen with a broad spectrum SPF of 15 or higher and other sun protection measures including: • Limit time in the sun, especially from 10 a.m. - 2 p.m. • Wear long-sleeve shirts, pants, hats and sunglasses. • Children under 6 months: Ask a doctor.

Other Information

• protect the product in this container from excessive heat and direct sun

Inactive Ingredients

Alcohol Denat., Isobutane, Isododecane, Diisopropyl Adipate, Mineral Oil, Phenylisopropyl Dimethicone, Polyglyceryl-3 Stearate/Isostearate/Dimer Dilinoleate Crosspolymer, Lauryl PEG-8 Dimethicone, Caprylyl Glycol, Methyl Dihydroabietate, Fragrance, Argania Spinosa Kernel Oil, Olea Europaea (Olive) Fruit Oil, Vitis Vinifera (Grape) Seed Oil, Ascorbyl Palmitate, Tocopheryl Acetate, Cocos Nucifera (Coconut) Oil, Glycine Soja (Soybean) Oil, Panthenol, Water, Psidium Guajava Fruit Extract, Plumeria Acutifolia Flower Extract, Passiflora Incarnata Fruit Extract, Mangifera Indica (Mango) Fruit Extract, Carica Papaya (Papaya) Fruit Extract, Aloe Barbadensis Leaf Extract, Daucus Carota Sativa (Carrot) Root Extract.

Questions or Comments?

Call 1-800-NO UV RAY, Mon-Fri

Principal Display Panel

HAWAIIAN
TROPIC(R)
SUNSCREEN DRY OIL SPRAY
PROTECTIVE
TANNING
ENHANCE TAN & MOISTURIZE
COCONUT OIL
30
DERM TESTED | VEGAN
BROAD SPECTRUM SPF 30 UVA/UVB
WATER RESISTANT (80 MINUTES)
NET WT 6.0 OZ (170g)